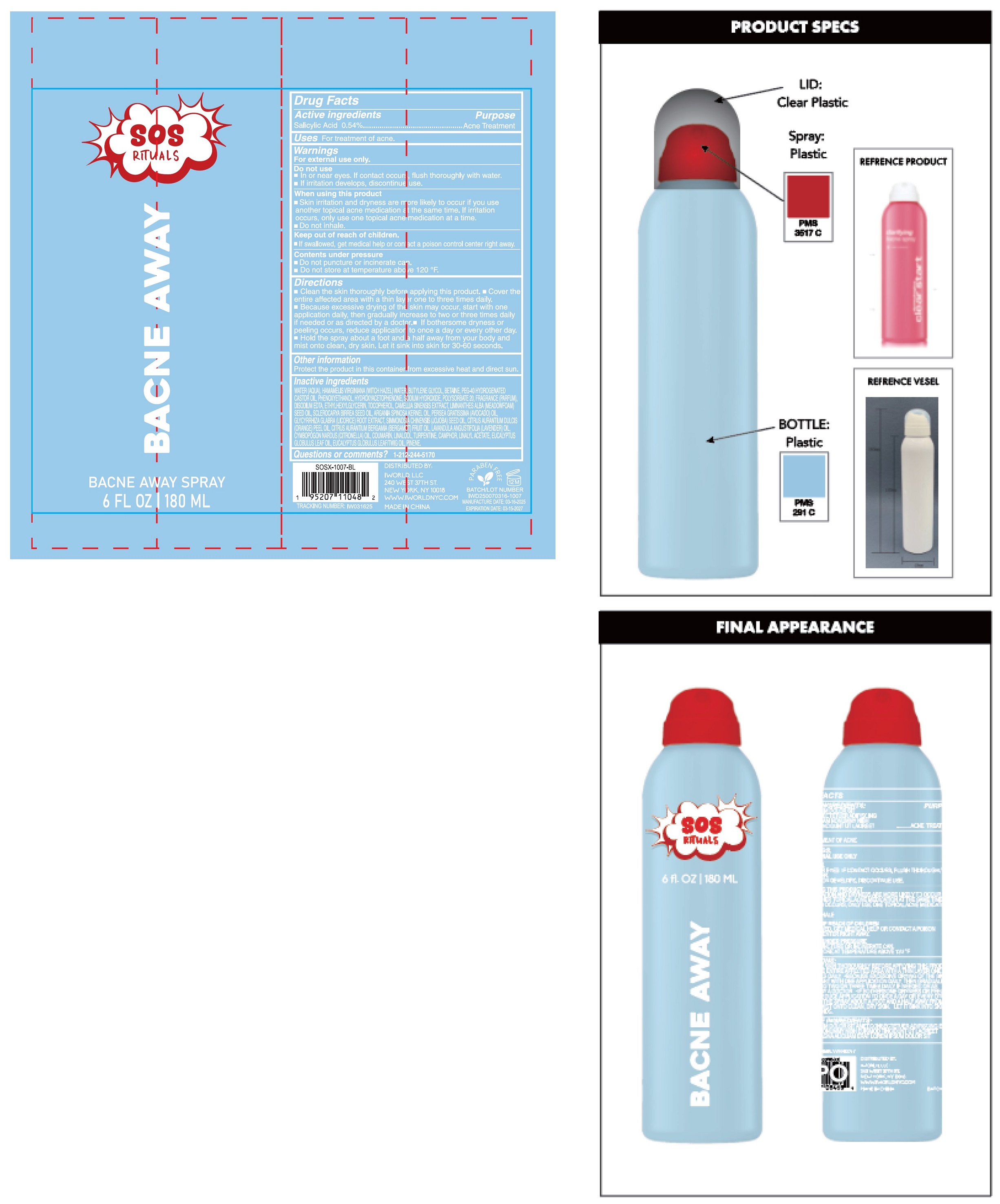 DRUG LABEL: SOS Rituals Bacne Away
NDC: 85179-006 | Form: LOTION
Manufacturer: I World LLC
Category: otc | Type: HUMAN OTC DRUG LABEL
Date: 20250314

ACTIVE INGREDIENTS: SALICYLIC ACID 5.4 mg/1 mL
INACTIVE INGREDIENTS: WATER; HAMAMELIS VIRGINIANA TOP WATER; BUTYLENE GLYCOL; BETAINE; POLYOXYL 40 HYDROGENATED CASTOR OIL; PHENOXYETHANOL; HYDROXYACETOPHENONE; SODIUM HYDROXIDE; POLYSORBATE 20; EDETATE DISODIUM; ETHYLHEXYLGLYCERIN; TOCOPHEROL; MEADOWFOAM SEED OIL; SCLEROCARYA BIRREA SEED OIL; ARGAN OIL; AVOCADO OIL; JOJOBA OIL; ORANGE OIL, COLD PRESSED; BERGAMOT OIL; LAVENDER OIL; CITRONELLA OIL; COUMARIN; LINALOOL, (+/-)-; TURPENTINE; LINALYL ACETATE; EUCALYPTUS OIL; PINENE

SOS Rituals Bacne Away Spray

Active ingredients

Salicylic Acid 0.54%

Purpose

Acne Treatment

Uses

For treatment of acne.

Warnings

For external use only.

Do not use

- In or near eyes. If contact occurs, flush thoroughly with water.
- If irritation develops, discontinue use.

When using this product

- Skin irritation and dryness are more likely to occur if you use another topical acne medication at the same time. If irritation occurs, only use one topical acne medication at a time.
- Do not inhale.

Keep out of reach of children.

- If swallowed, get medical help or contact a poison control center right away.

contents under pressure

- Do not puncture or incinerate can.
- Do not store at temperature above 120 °F.

Directions

- Clean the skin thoroughly before applying this product.
- Cover the entire affected area with a thin layer one to three times daily.
- Because exessive drying of the skin may occur,start with one application daily,then gradually increase to two or three times daily if needed or as directed by a doctor.
- If bothersome dryness or peeling occurs, reduce application to once a day or every other day.
- Hold the spray about a foot and a half away from your body and mist onto clean, dry skin. Let it sink into skin for 30-60 seconds.

Other information

Protect the product in this container from excessive heat and direct sun.

Inactive ingredients

WATER (AQUA), HAMAMELIS VIRGNIANA (WITCH HAZEL) WATER, BUTYLENE GLYCOL, BETAINE, PEG-40 HYDROGENATED CASTOR OIL, PHENOXYETHANOL, HYDROXYACETOPHENONE, SODIUM HYDROXIDE, POLYSORBATE 20, FRAGRANCE (PARFUM), DISODIUM EDTA, ETHYLHEXYLGLYCERIN, TOCOPHEROL, CAMELLIA SINESIS EXTRACT, LIMANTHES ALBA (MEADOWFOAM) SEED OIL, SCLEROCARYA BIRREA SEED OIL, ARGANIA SPINOSA KERNEL OIL, PERSEA GRATISSIMA (AVOCADO) OIL, GLYCYRRHIZA GLABRA (LICORICE) ROOT EXTRACT, SIMMONDSIA CHINENSIS (JOJOBA) SEED OIL, CITRUS AURANTIUM DULCIS (ORANGE) PEEL OIL, CITRUS AURANTIUM BERGAMIA (BERGAMOT) FRUIT OIL, LAVANDULA ANGUSTIFOLIA (LAVENDER) OIL, CYMBOPOGON NARDUS (CITRONELLA) OIL, COUMARIN, LINALOOL, TURPENTINE, CAMPHOR, LINALYL ACETATE, EUCALYPTUS GLOBULUS LEAF/TWiG OIL, PINENE.

Questions or comments?

1-212-244-5170